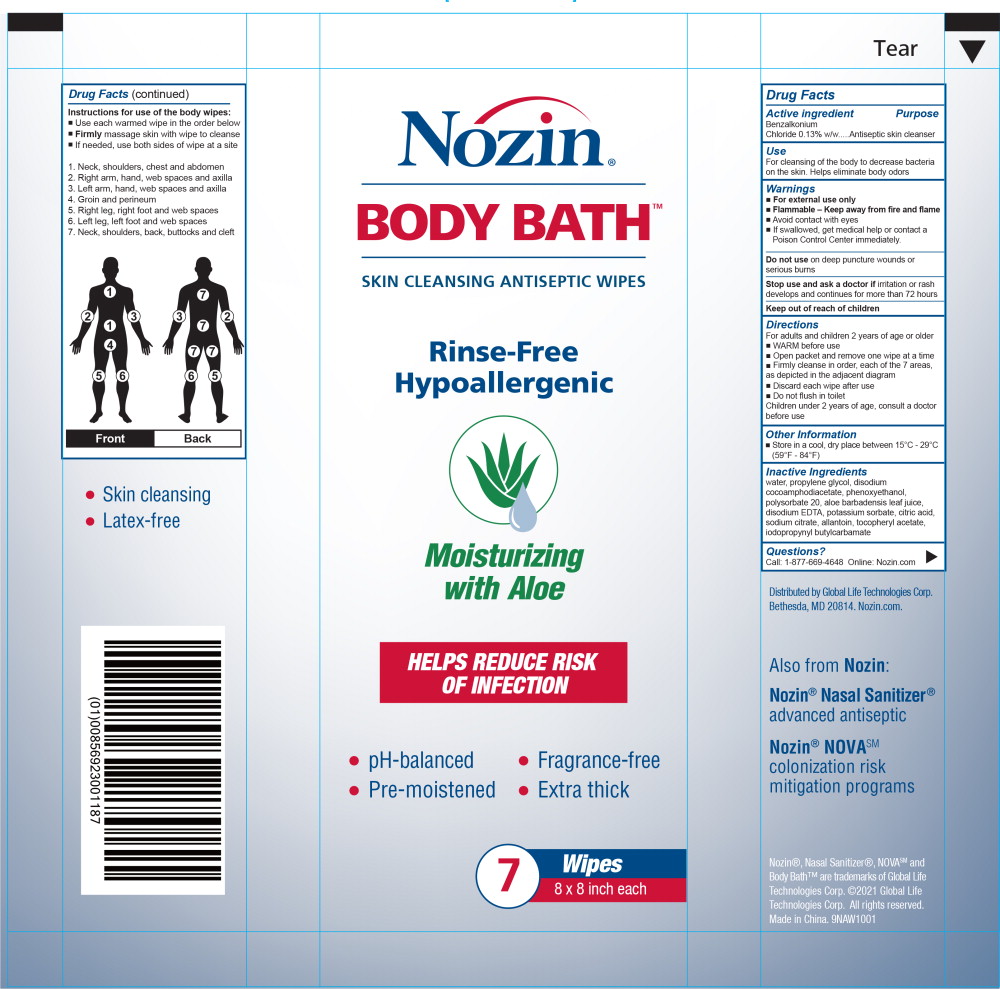 DRUG LABEL: Nozin Body Bath (Skin Cleansing Antiseptic Wipes)
NDC: 82539-013 | Form: CLOTH
Manufacturer: Global Life Technologies Corp.
Category: otc | Type: HUMAN OTC DRUG LABEL
Date: 20211201

ACTIVE INGREDIENTS: Benzalkonium Chloride 0.13 mg/100 mg
INACTIVE INGREDIENTS: water; propylene glycol; disodium cocoamphodiacetate; phenoxyethanol; polysorbate 20; aloe vera leaf; edetate disodium; potassium sorbate; citric acid monohydrate; sodium citrate; allantoin; .alpha.-tocopherol acetate; iodopropynyl butylcarbamate; alcohol

Drug Facts

Active ingredient

Benzalkonium Chloride 0.13% w/w

Purpose

Antiseptic skin cleanser

Use

For cleansing of the body to decrease bacteria on the skin. Helps eliminate body odors

Warnings

- For external use only
- Flammable - Keep away from fire and flame
- Avoid contact with eyes
- If swallowed, get medical help or contact a Poison Control Center immediately.

Do not use on deep puncture wounds or serious burns

Stop use and ask a doctor if irritation or rash develops and continues for more than 72 hours

Directions

For adults and children 2 years of age or older

- WARM before use
- Open packet and remove one wipe at a time
- Firmly cleanse in order, each of the 7 areas, as depicted in the adjacent diagram
- Discard each wipe after use
- Do not flush in toilet

Children under 2 years of age, consult a doctor before use

Other Information

- Store in a cool, dry place between 15°C - 29°C (59°F - 84°F)

Inactive Ingredients

water, propylene glycol, disodium cocoamphodiacetate, phenoxyethanol, polysorbate 20, aloe barbadensis leaf juice, disodium EDTA, potassium sorbate, citric acid, sodium citrate, allantoin, tocopheryl acetate, iodopropynyl butylcarbamate

Questions?

Call: 1-877-669-4648 Online: Nozin.com

Instructions for use of the body wipes:

- Use each warmed wipe in the order below
- Firmly massage skin with wipe to cleanse
- If needed, use both sides of wipe at a site

1. Neck, shoulders, chest and abdomen
2. Right arm, hand, web spaces and axilla
3. Left arm, hand, web spaces and axilla
4. Groin and perineum
5. Right leg, right foot and web spaces
6. Left leg, left foot and web spaces
7. Neck, shoulders, back, buttocks and cleft

Principal Display Panel - 24 Packets Case Label

Nozin®

BODY BATH™

SKIN CLEANSING ANTISEPTIC WIPES

Rinse-Free
Hypoallergenic

Moisturizing
with Aloe

HELPS REDUCE RISK
OF INFECTION

- pH-balanced
- Pre-moistened
- Fragrance-free
- Extra thick

7 Wipes

8 x 8 inch each